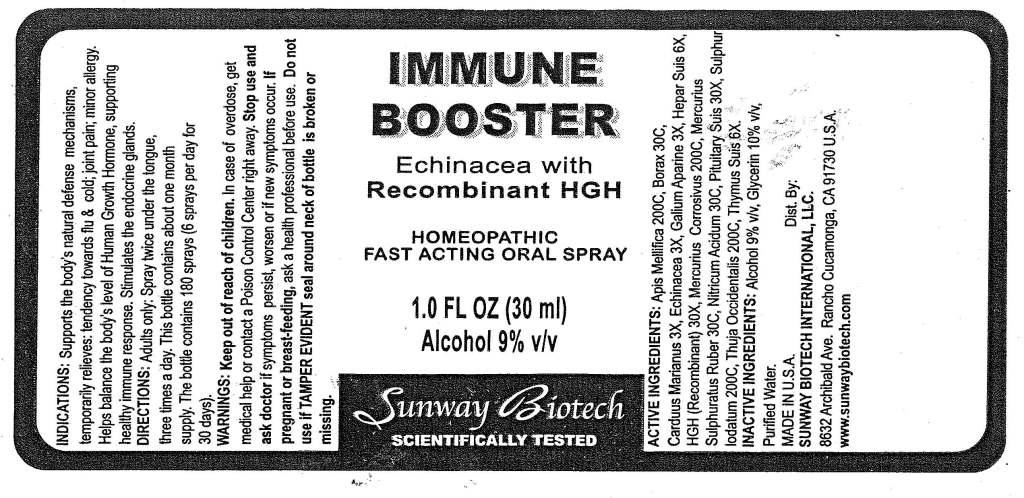 DRUG LABEL: Immune Booster
NDC: 50845-0114 | Form: SPRAY
Manufacturer: Liddell Laboratories, Inc.
Category: homeopathic | Type: HUMAN OTC DRUG LABEL
Date: 20101215

ACTIVE INGREDIENTS: APIS MELLIFERA 200 [hp_C]/1 mL; SODIUM BORATE 30 [hp_C]/1 mL; SILYBUM MARIANUM SEED 3 [hp_X]/1 mL; ECHINACEA 3 [hp_X]/1 mL; GALIUM APARINE 3 [hp_X]/1 mL; PORK LIVER 6 [hp_X]/1 mL; SOMATROPIN 30 [hp_X]/1 mL; MERCURIC CHLORIDE 200 [hp_C]/1 mL; MERCURIC SULFIDE 30 [hp_C]/1 mL; NITRIC ACID 30 [hp_C]/1 mL; SUS SCROFA PITUITARY GLAND 30 [hp_X]/1 mL; SULFUR IODIDE 200 [hp_C]/1 mL; THUJA OCCIDENTALIS LEAFY TWIG 200 [hp_C]/1 mL; SUS SCROFA THYMUS 6 [hp_X]/1 mL
INACTIVE INGREDIENTS: WATER; ALCOHOL; GLYCERIN

Immune Booster

ACTIVE INGREDIENT

ACTIVE INGREDIENTS: Apis Mellifica 200C, Borax 30C, Carduus marianus 3X, Echinacea 3X, Galium aparine 3X, Hepar suis 6X, HGH 30X, Mercurius corrosivus 200C, Mercurius sulphuratus ruber 20C, Nitricum acidum 30C, Putuitary suis 30X, Sulphur iodatum 200C, Thuja occidentalis 200C, Thymus suis.

PURPOSE

INDICATIONS: Supports the body's natural defense mechanisms, temporarily relieves: tendency towards flu and cold; joint pain; minor allergy. Helps balance the body's level of Human Growth Hormone, supporting healthy immune response. Stimulates the endocrine glands.

WARNINGS

WARNINGS: Keep out of reach of children. In case of overdose, get medical help or contact a Poison Control Center right away.

Stop use and ask doctor is symptoms persist, worsen or if new symptoms occur.

If pregnant or breast-feeding, ask a health professional before use.

Do not use if TAMPER EVIDENT seal around neck of bottle is broken or missing.

DOSAGE AND ADMINISTRATION

DIRECTIONS: Adults only: Spray twice under the tongue, three times a day. This bottle contains about one month supply. The bottle contains 180 sprays (6 sprays per day for 30 days).

INACTIVE INGREDIENT

INACTIVE INGREDIENTS: Alcohol 9% v/v, Glycerin 10% v/v, Purified water.

KEEP OUT OF REACH OF CHILDREN. In case of overdose, get medical help or contact a Poison Control Center right away.

INDICATIONS AND USAGE

INDICATIONS: Supports the body's natural defense mechanisms, temporarily relieves: tendency towards flu and cold; joint pain; minor allergy. Helps balance the body's level of Human Growth Hormone, supporting healthy immune response. Stimulates the endocrine glands.

QUESTIONS

MADE IN U.S.A.

Dist. By:

SUNWAY BIOTECH INTERNATIONAL, LLC.

8632 Archibald Ave.

Rancho Cucamonga, CA 91730 U.S.A.

www.sunwaybiotech.com

PACKAGE LABEL

IMMUNE BOOSTER

Echinacea with Recombinant HGH

HOMEOPATHIC

FAST ACTING ORAL SPRAY

1.0 FL OZ (30 ml)

SUNWAY BIOTECH

SCIENTIFICALLY TESTED